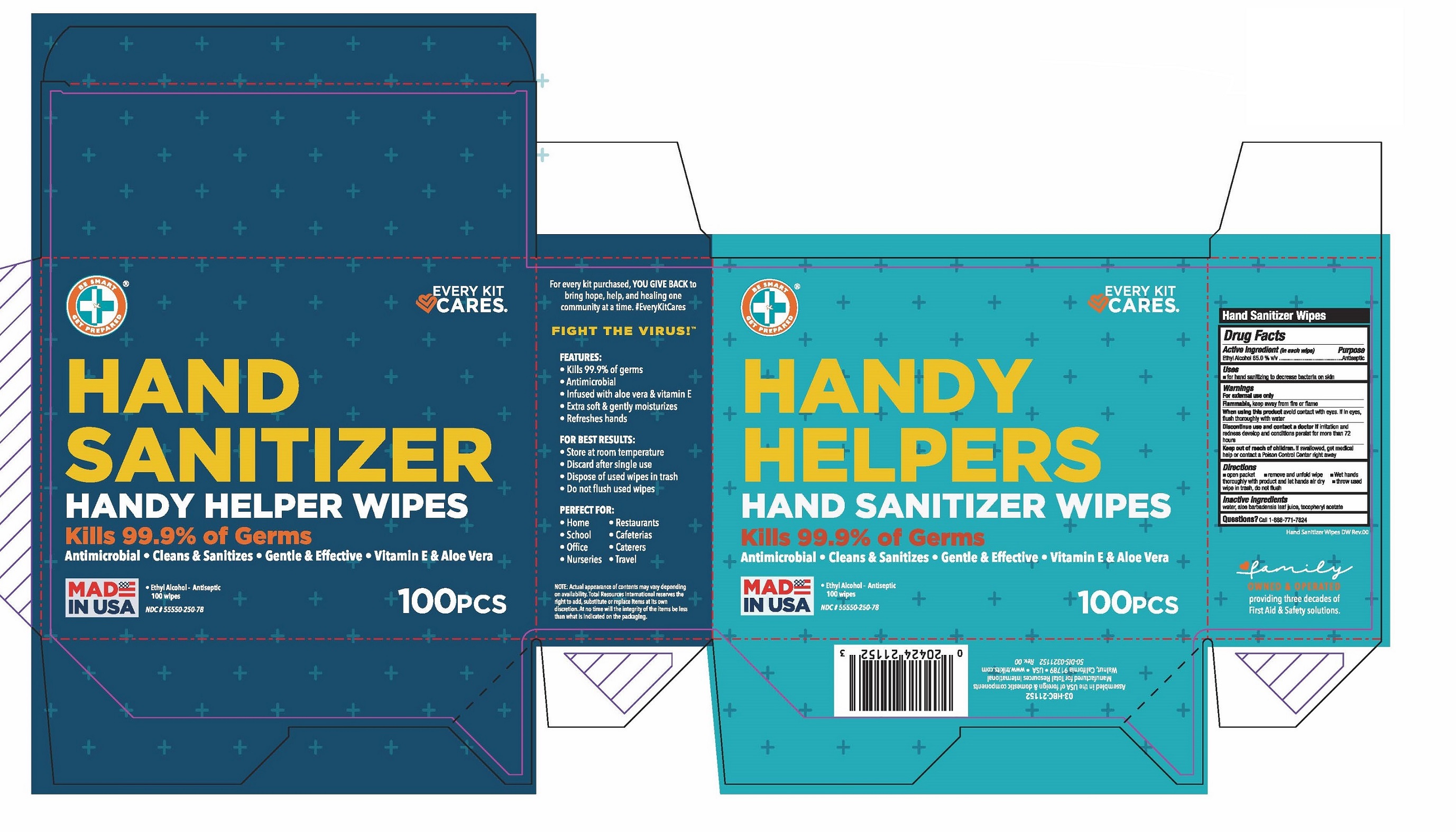 DRUG LABEL: Hand Sanitizer Handy Helper Wipes
NDC: 55550-250 | Form: CLOTH
Manufacturer: Total Resources International
Category: otc | Type: HUMAN OTC DRUG LABEL
Date: 20231222

ACTIVE INGREDIENTS: ALCOHOL 65 mL/100 mL
INACTIVE INGREDIENTS: ALOE VERA LEAF; .ALPHA.-TOCOPHEROL ACETATE, DL-; WATER

Total Resources Hand Sanitizer

Active Ingredeint

Ethyl Alcohol 65% v/v

Purpose

Antiseptic

Uses

- For hand sanitizing to decrease bacteria on skin.
- recommended for repeated use

Warnings

- For external use only
- Flammable, keep away from flame or fire
- When using this product avoid contact with eyes. If in eyes, flush thoroughly with water
- Discontinue use and contact a doctor if irritation and redness develop and conditions persist for more than 72 hours

Keep Out Of Reach Of Children

If swallowed get medical help or contact a poison control center right away

Directions

- Open packet
- remove and unfold wipe
- wet hands thoroughly with product and let hands dry
- throw used wipe in trash, do not flush

Inactive ingredeints

Water, Aloe barbadensis leaf juice, Tocopheryl Acetate

Label

HAND
SANITIZER

Handy Helper wipes

Kills 99.99% of Germs
Antimicrobial • Cleans • Sanitizes • Gentle
Effective • Vitamin E • Aloe Vera

•Ethyl Alcohol • Antiseptic

100PCS

Family Owned and Operated Providing three decades of First Aid & Safety Solutions

For every kit purchased, YOU GIVE

BACK to bring hope, help, and

healing one community at a time.

#EveryKitCares

FEATURES:

• Antimicrobial

• Kills 99.99% of germs

• Dries in seconds

• Infused with aloe vera & vitamin E

• Extra soft & gently moisturizes

• Refreshes hands

FOR BEST RESULTS:

• Discard after single use

• Dispose of used wipes in trash

• Do not flush used wipes

• Store at room temperature

PERFECT FOR:

• Home

• School

• Office

• Nuseries

• Restaurants

• Cafeterias

• Caterers

• Travel

Made in USA